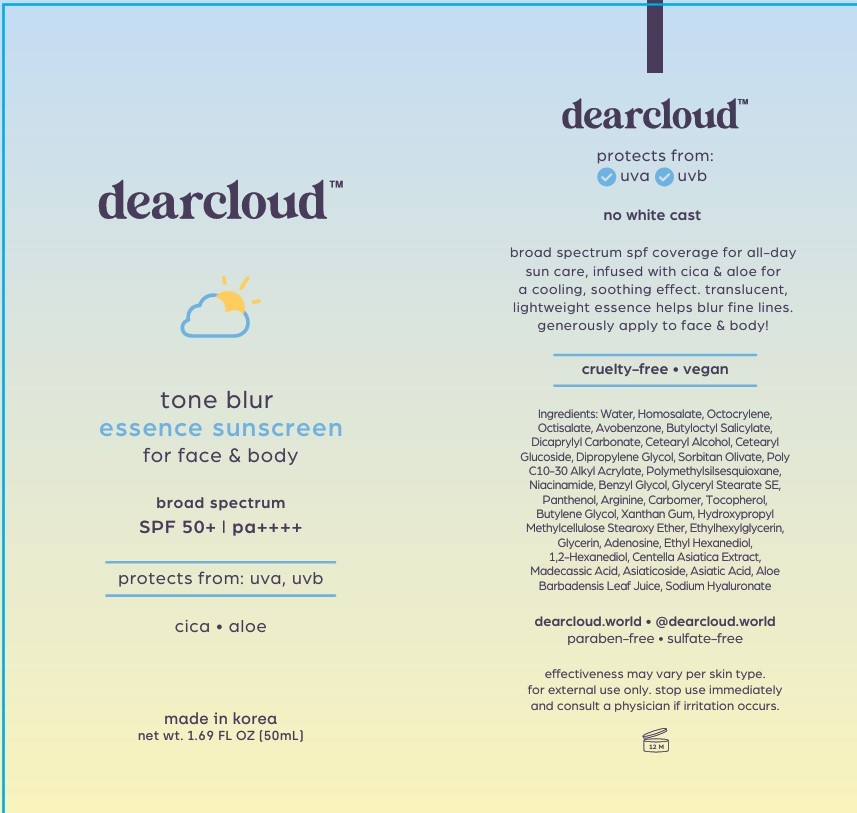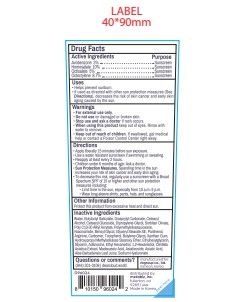 DRUG LABEL: Tone Blur Essence Sunscreen
NDC: 84326-124 | Form: CREAM
Manufacturer: RBGROUP Co., Ltd
Category: otc | Type: HUMAN OTC DRUG LABEL
Date: 20251117

ACTIVE INGREDIENTS: AVOBENZONE 1.5 g/50 mL; OCTISALATE 2.5 g/50 mL; OCTOCRYLENE 4.35 g/50 mL; HOMOSALATE 5 g/50 mL
INACTIVE INGREDIENTS: BUTYLOCTYL SALICYLATE; CETEARYL GLUCOSIDE; ADENOSINE; ASIATIC ACID; .ALPHA.-TOCOPHEROL, DL-; BEHENYL ACRYLATE POLYMER; NIACINAMIDE; ETHYLENE GLYCOL MONOBENZYL ETHER; GLYCERIN; MADECASSIC ACID; HYPROMELLOSE 2208 0.45% STEAROXY ETHER; POLYACRYLIC ACID (800000 MW); ASIATICOSIDE; GLYCERYL STEARATE SE; ARGININE; HYALURONATE SODIUM; WATER; DICAPRYLYL CARBONATE; CETOSTEARYL ALCOHOL; SORBITAN OLIVATE; BUTYLENE GLYCOL; XANTHAN GUM; ETHYLHEXYLGLYCERIN; CENTELLA ASIATICA TRITERPENOIDS; ALOE VERA LEAF; DIPROPYLENE GLYCOL; PANTHENOL; POLYMETHYLSILSESQUIOXANE (4.5 MICRONS); ETHOHEXADIOL; 1,2-HEXANEDIOL

84326-124 Tone Blur Essence Sunscreen

ACTIVE INGREDIENT

Avobenzone 3.0%

Homosalate 10.0%

Octisalate 5.0%

Octocrylene 8.7%

PURPOSE

Sunscreen

INDICATIONS AND USAGE

■ Helps prevent sunburn.

■ If used as directed with other sun protection measures (See Directions), decreases the risk of skin cancer and early skin aging caused by the sun.

WARNINGS

For external use only

DO NOT USE

■ on damaged skin or broken skin

WHEN USING

this product ■ keep out of eyes. Rinse with water to remove.

STOP USE

and ask a doctor if rash occurs.

KEEP OUT OF REACH OF CHILDREN

If swallowed, get medical help or contact a Poison Control Center right away.

OTHER SAFETY INFORMATION

■ Protect this product from excessive heat and direct sun.

Directions
■ Apply liberally 15 minutes before sun exposure.

■ Use a water resistant sunscreen if swimming or swating.

■ Reapply at least every 2 hours.

■ Children under 6 months of age: Ask a doctor.

■ Sun Protection Measures Spending time in the sun increases your risk of skin cancer and early skin aging. To decrease this risk, regularly use a sunscreen with a Broad Spectrum SPF value of 15 or higher and other sun protection measures including: ■ Limit time in the sun, especially from 10a.m. - 2 p.m. ■ Wear long-sleeve shirts, pants, hats, and sunglasses.

INACTIVE INGREDIENT

Water, Butyloctyl Salicylate, Dicaprylyl Carbonate, Cetearyl Alcohol, Cetearyl Glucosidde, Dipropylene Glycol, Sorbitan Olivate, Poly C10-30 Alkyl Acrylate, Polymethylsilsesquioxane, Niacinamide, Benzyl Glycol, Glyceryl Stearate SE, Panthenol, Arginine, Carbomer, Tocopherol, Butylene Glycol, Xanthan Gum, Hydroxypropyl Methylcellulose Stearoxy Ether, Ethylhexylglycerin, Glycerin, Adenosine, Ethyl Hexanediol, 1,2-Hexanediol, Centella Asiatica Extract, Madecassic Acid, Asiaticoside, Asiatic Acid, Aloe Barbadensis Leaf Juice, Sodium Hyaluronate